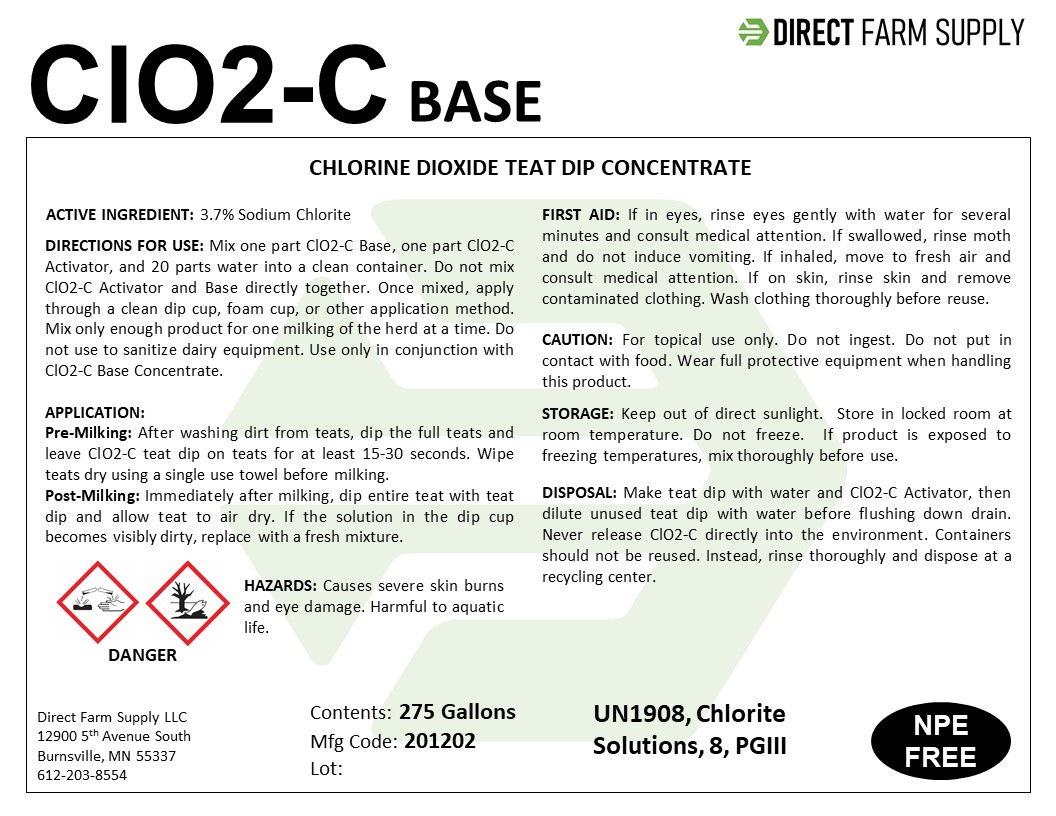 DRUG LABEL: ClO2-C Base
NDC: 86143-002 | Form: LIQUID
Manufacturer: Direct Farm Supply
Category: animal | Type: OTC ANIMAL DRUG LABEL
Date: 20210808

ACTIVE INGREDIENTS: SODIUM CHLORITE 37 mg/1 mL

ClO2-C Base

FIRST AID

If in eyes, rinse eyes gently with water for several minutes and consult medical attention. If swallowed, rinse moth and do not induce vomiting. If inhaled, move to fresh air and consult medical attention. If on skin, rinse skin and remove contaminated clothing. Wash clothing thoroughly before reuse.

DIRECTIONS FOR USE

Mix one part ClO2-C Base, one part ClO2-C Activator, and 20 parts water into a clean container. Do not mix ClO2-C Activator and Base directly together. Once mixed, apply through a clean dip cup, foam cup, or other application method. Mix only enough product for one milking of the herd at a time. Do not use to sanitize dairy equipment. Use only in conjunction with ClO2-C Base Concentrate.

APPLICATION:

Pre-Milking: After washing dirt from teats, dip the full teats and leave ClO2-C teat dip on teats for at least 15-30 seconds. Wipe teats dry using a single use towel before milking.
Post-Milking: Immediately after milking, dip entire teat with teat dip and allow teat to air dry. If the solution in the dip cup becomes visibly dirty, replace with a fresh mixture.

STORAGE

Keep out of direct sunlight. Store in locked room at room temperature. Do not freeze. If product is exposed to freezing temperatures, mix thoroughly before use.

DISPOSAL

Make teat dip with water and ClO2-C Activator, then dilute unused teat dip with water before flushing down drain. Never release ClO2-C directly into the environment. Containers should not be reused. Instead, rinse thoroughly and dispose at a recycling center.

GENERAL CAUTION

For topical use only. Do not ingest. Do not put in contact with food. Wear full protective equipment when handling this product.